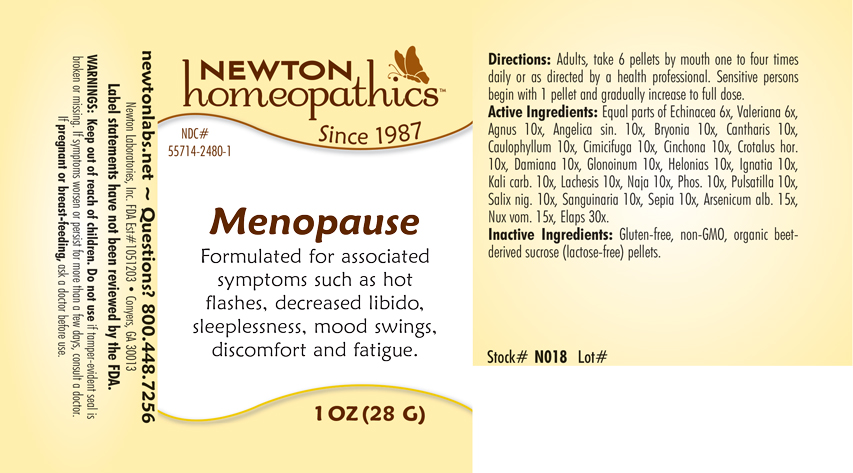 DRUG LABEL: Menopause
NDC: 55714-2480 | Form: PELLET
Manufacturer: Newton Laboratories, Inc.
Category: homeopathic | Type: HUMAN OTC DRUG LABEL
Date: 20250207

ACTIVE INGREDIENTS: MICRURUS CORALLINUS VENOM 30 [hp_X]/1 g; CHASTE TREE FRUIT 10 [hp_X]/1 g; ANGELICA SINENSIS ROOT 10 [hp_X]/1 g; ARSENIC TRIOXIDE 15 [hp_X]/1 g; BRYONIA ALBA ROOT 10 [hp_X]/1 g; LYTTA VESICATORIA 10 [hp_X]/1 g; CAULOPHYLLUM THALICTROIDES ROOT 10 [hp_X]/1 g; BLACK COHOSH 10 [hp_X]/1 g; CINCHONA OFFICINALIS BARK 10 [hp_X]/1 g; CROTALUS HORRIDUS HORRIDUS VENOM 10 [hp_X]/1 g; TURNERA DIFFUSA LEAFY TWIG 10 [hp_X]/1 g; NITROGLYCERIN 10 [hp_X]/1 g; CHAMAELIRIUM LUTEUM ROOT 10 [hp_X]/1 g; STRYCHNOS IGNATII SEED 10 [hp_X]/1 g; POTASSIUM CARBONATE 10 [hp_X]/1 g; LACHESIS MUTA VENOM 10 [hp_X]/1 g; NAJA NAJA VENOM 10 [hp_X]/1 g; STRYCHNOS NUX-VOMICA SEED 15 [hp_X]/1 g; PHOSPHORUS 10 [hp_X]/1 g; VALERIAN 6 [hp_X]/1 g; ANEMONE PULSATILLA 10 [hp_X]/1 g; SALIX NIGRA BARK 10 [hp_X]/1 g; SANGUINARIA CANADENSIS ROOT 10 [hp_X]/1 g; SEPIA OFFICINALIS JUICE 10 [hp_X]/1 g; ECHINACEA, UNSPECIFIED 6 [hp_X]/1 g
INACTIVE INGREDIENTS: SUCROSE

Menopause 2480P

INDICATIONS & USAGE SECTION

Formulated for associated symptoms such as hot flashes, decreased libido, sleeplessness, mood swings, discomfort and fatigue.

DOSAGE & ADMINISTRATION SECTION

Directions: Adults, take 6 pellets by mouth one to four times daily or as directed by a health professional. Sensitive persons begin with 1 pellet and gradually increase to full dose.

OTC - ACTIVE INGREDIENT SECTION

Equal parts of Echinacea 6x, Valeriana officinalis 6x, Agnus castus 10x, Angelica sinensis radix 10x, Bryonia 10x, Cantharis 10x, Caulophyllum thalictroides 10x, Cimicifuga racemosa 10x, Cinchona officinalis 10x, Crotalus horridus 10x, Damiana 10x, Glonoinum 10x, Helonias dioica 10x, Ignatia amara 10x, Kali carbonicum 10x, Lachesis mutus 10x, Naja tripudians 10x, Phosphorus 10x, Pulsatilla 10x, Salix nigra 10x, Sanguinaria canadensis 10x, Sepia 10x, Arsenicum album 15x, Nux vomica 15x, Elaps corallinus 30x.

OTC - PURPOSE SECTION

Formulated for associated symptoms such as hot flashes, decreased libido, sleeplessness, mood swings, discomfort and fatigue.

INACTIVE INGREDIENT SECTION

Inactive Ingredients: Gluten-free, non-GMO, organic beet-derived sucrose (lactose-free) pellets.

QUESTIONS SECTION

newtonlabs.net – Questions? 800.448.7256

Newton Laboratories, Inc. FDA Est # 1051203 - Conyers, GA 30013

WARNINGS SECTION

WARNINGS: Keep out of reach of children. Do not use if tamper-evident seal is broken or missing. If symptoms worsen or persist for more than a few days, consult a doctor. If pregnant or breast-feeding, ask a doctor before use.

OTC - PREGNANCY OR BREAST FEEDING SECTION

If pregnant or breast-feeding, ask a doctor before use.

OTC - KEEP OUT OF REACH OF CHILDREN SECTION

Keep out of reach of children